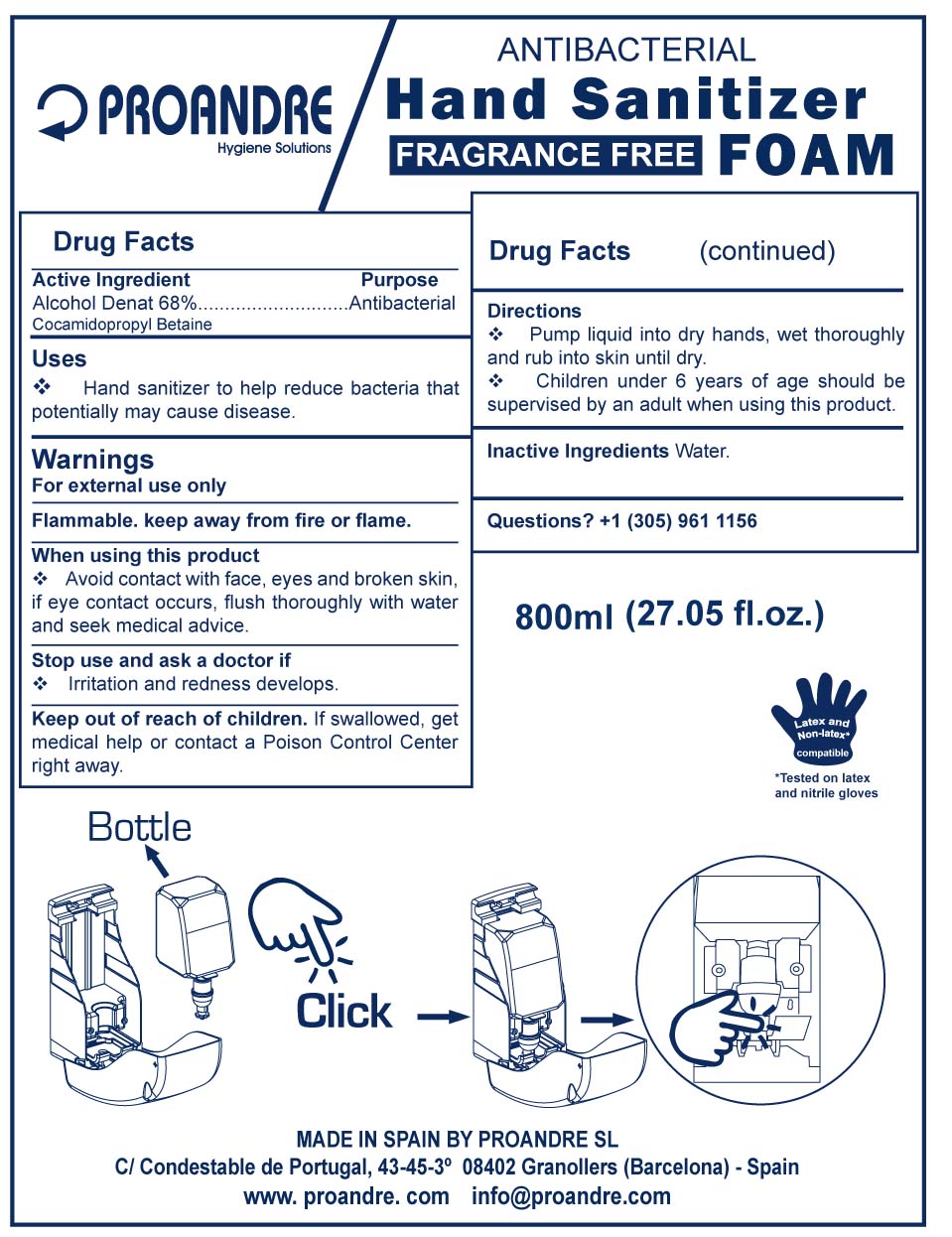 DRUG LABEL: Proandre
NDC: 70028-003 | Form: AEROSOL, FOAM
Manufacturer: Proandre SL
Category: otc | Type: HUMAN OTC DRUG LABEL
Date: 20170620

ACTIVE INGREDIENTS: ALCOHOL 40 mg/1 mL
INACTIVE INGREDIENTS: COCAMIDOPROPYL BETAINE 10 mg/1 mL; WATER 50 mg/1 mL

Antibacterial Handsanitizer Foam

Active Ingredient

Active Ingredient Purpose

Alcohol Denat 68%............ Antibacterial

Uses

* Hand Sanitizer to help reduce bacteria that potentially may cause disease

Warnings

For external use only

Flammable. Keep away from fire or flame

When using this product

* Avoid contact with face, eyes and broken skin.

If eye contact occurs, flush thoroughly with water

and seek medical advice.

Stop use and ask a doctor if

* Irritation and redness develops

Keep out of reach of children. If swallowed, get medical help

or contact a Poison Control Center right away.

Directions

* Pump liquid into dry hands, wet thoroughly and rub

into skin until dry.

* Children under 6 years of age should be supervised by an

adult when using this product.

Inactive Ingredients

Water, Cocamidopropyl betaine

Questions?

1(305) 961 1156

Uses

Hand sanitizer to help reduce bacteria on hands. Avoid

contact with broken skin

Antibacterial Hand Sanitizer Foam

Fragrance Free